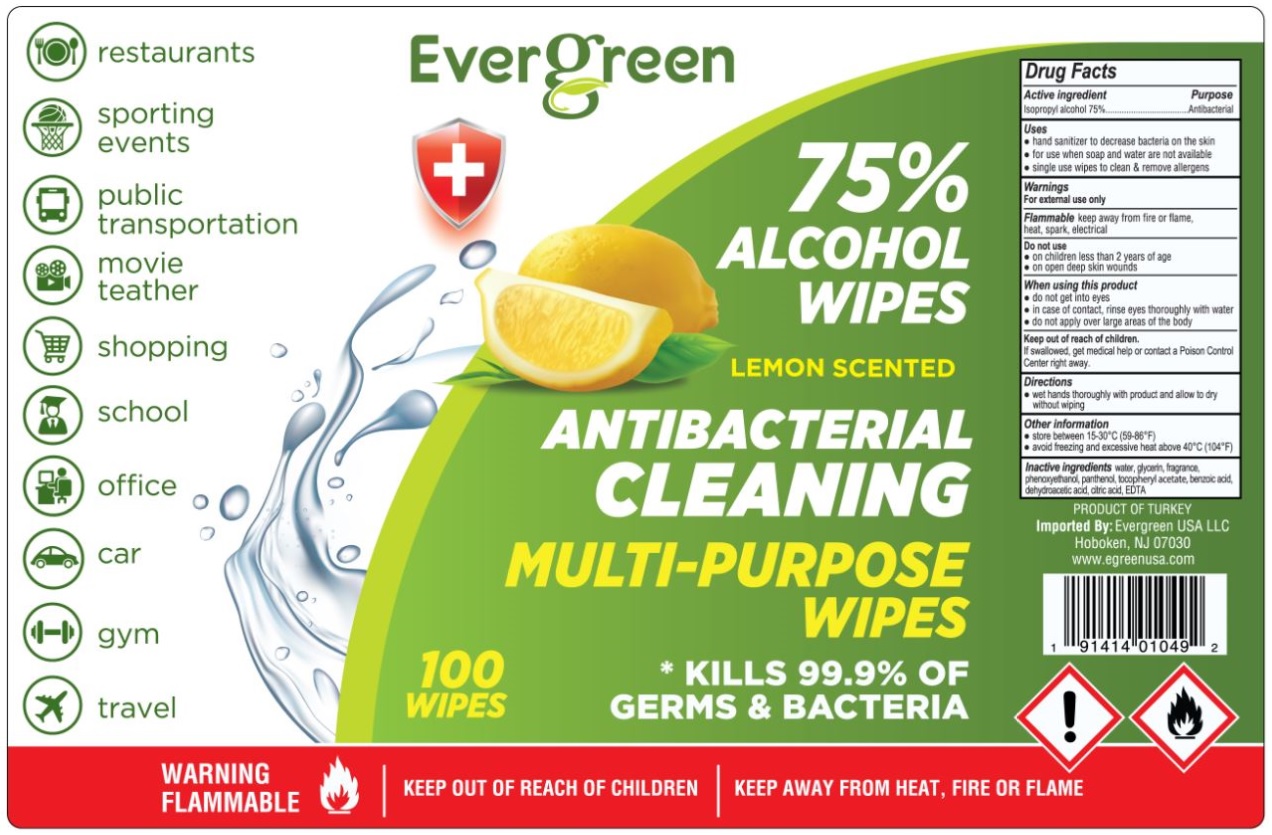 DRUG LABEL: Evergreen LEMON SCENTED ANTIBACTERIAL CLEANING MULTI-PURPOSE WIPES
NDC: 79881-030 | Form: CLOTH
Manufacturer: ELA KOZMETIK VE HIJYENIK URUNLERI SANAYI TICARET LIMITED SIRKETI
Category: otc | Type: HUMAN OTC DRUG LABEL
Date: 20200930

ACTIVE INGREDIENTS: ISOPROPYL ALCOHOL 75 mL/100 mL
INACTIVE INGREDIENTS: WATER; GLYCERIN; PHENOXYETHANOL; PANTHENOL; .ALPHA.-TOCOPHEROL ACETATE; BENZOIC ACID; DEHYDROACETIC ACID; CITRIC ACID MONOHYDRATE; EDETIC ACID

Evergreen ANTIBACTERIAL CLEANING MULTI-PURPOSE WIPES

Active ingredient

Isopropyl alcohol 75%

Purpose

Antibacterial

Uses

• hand sanitizer to decrease bacteria on the skin

• For use when soap and water are not available

• single use wipes to clean & remove allergens

Warnings

For external use only

Flammable keep away from fire or flame, heat, spark, electrical

Do not use

• on children less than 2 years of age

• on open deep skin wounds

When using this product

• do not get into eyes.

• in case of contact, rinse eyes thoroughly with water

• do not apply over large areas of the body

Keep out of reach of children.

If swallowed, get medical help or contact a Poison Control Center right away

Directions

• wet hands thoroughly with product and allow to dry without wiping

Other information

• store between 15-30°C (59-86°F)

• avoid freezing and excessive heat above 40°C (104°F)

INACTIVE INGREDIENT

Inactive ingredients water, glycerin, fragrance, phenoxyethanol, panthenol, tocopheryl acetate, benzoic acid, dehydroacetic acid, citric acid, EDTA

* KILLS 99.9% OF GERMS & BACTERIA

WARNING FLAMMABLE

KEEP OUT OF REACH OF CHILDREN

KEEP AWAY FROM HEAT, FIRE OR FLAME

restaurants

sporting events

public transportation

movie theatre

shopping

school

office

car

gym

travel

PRODUCT OF TURKEY

Imported By: Evergreen USA LLC

Hoboken, NJ 07030

www.egreenusa.com